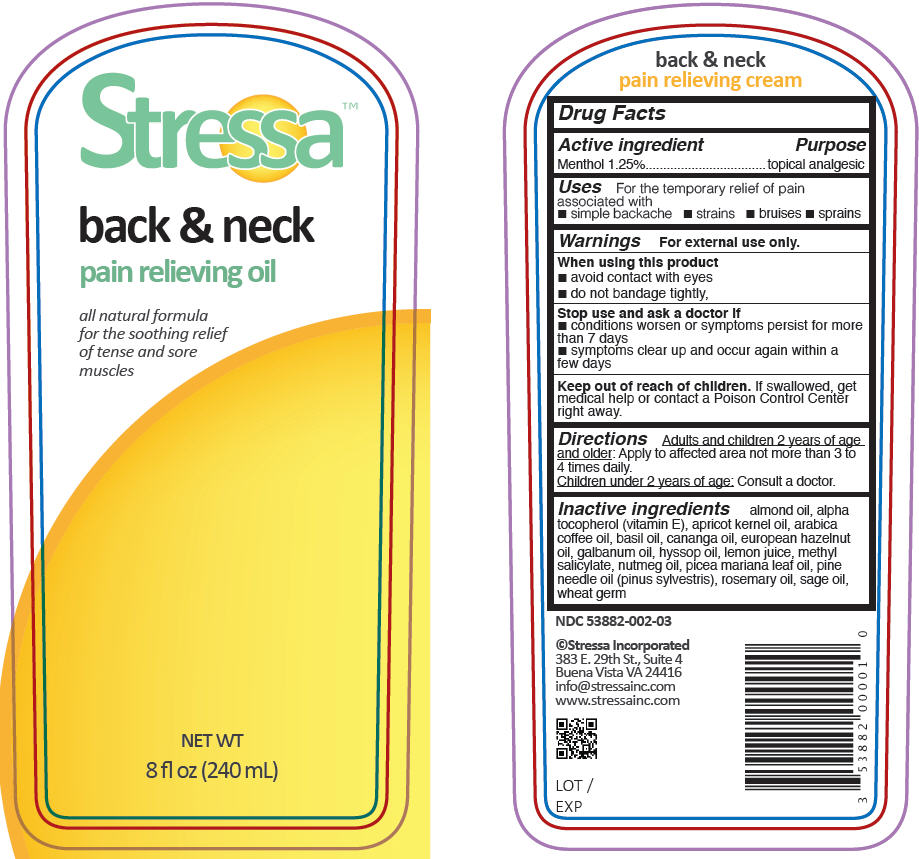 DRUG LABEL: Stressa Back and Neck Pain Relieving
NDC: 53882-002 | Form: OIL
Manufacturer: Stressa Incorporated
Category: otc | Type: HUMAN OTC DRUG LABEL
Date: 20140804

ACTIVE INGREDIENTS: Menthol 1 g/93 mL
INACTIVE INGREDIENTS: ALMOND OIL; APRICOT KERNEL OIL; BASIL OIL; ARABICA COFFEE OIL; GALBANUM OIL; EUROPEAN HAZELNUT OIL; HYSSOP OIL; LEMON OIL; NUTMEG OIL; ROSEMARY OIL; SAGE OIL; PINE NEEDLE OIL (PINUS SYLVESTRIS); PICEA MARIANA LEAF OIL; .ALPHA.-TOCOPHEROL; WHEAT GERM; METHYL SALICYLATE; CANANGA OIL

Stressa™ Back & Neck Pain Relieving Oil

Drug Facts

Active ingredient

Menthol 1.25%

Purpose

topical analgesic

Uses

For the temporary relief of pain associated with

- simple backache
- strains
- bruises
- sprains

Warnings

For external use only.

When using this product

- avoid contact with eyes
- do not bandage tightly,

Stop use and ask a doctor if

- conditions worsen or symptoms persist for more than 7 days
- symptoms clear up and occur again within a few days

Keep out of reach of children. If swallowed, get medical help or contact a Poison Control Center right away.

Directions

Adults and children 2 years of age and older: Apply to affected area not more than 3 to 4 times daily.

Children under 2 years of age: Consult a doctor.

Inactive ingredients

almond oil, alpha tocopherol (vitamin E), apricot kernel oil, arabica coffee oil, basil oil, cananga oil, european hazelnut oil, galbanum oil, hyssop oil, lemon juice, methyl salicylate, nutmeg oil, picea mariana leaf oil, pine needle oil (pinus sylvestris), rosemary oil, sage oil, wheat germ

PRINCIPAL DISPLAY PANEL - 240 mL Bottle Label

Stressa™

back & neck
pain relieving oil

all natural formula
for the soothing relief
of tense and sore
muscles

NET WT
8 fl oz (240 mL)